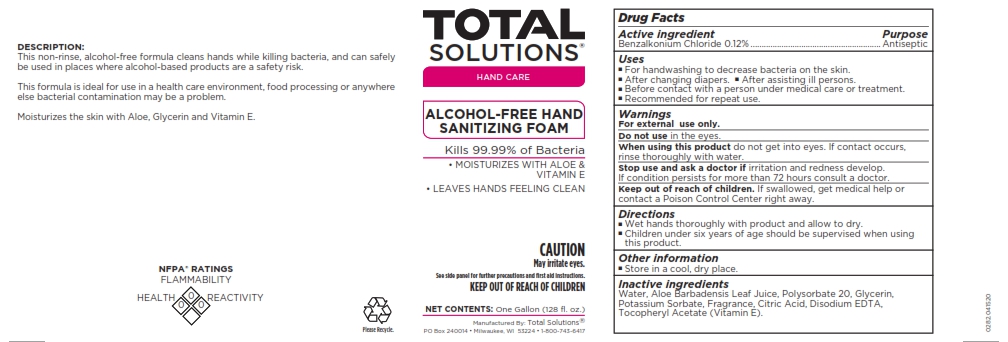 DRUG LABEL: Total Solutions Alcohol-Free Hand Sanitizing Foam
NDC: 62819-282 | Form: LIQUID
Manufacturer: Athea Laboratories, Inc.
Category: otc | Type: HUMAN OTC DRUG LABEL
Date: 20250101

ACTIVE INGREDIENTS: BENZALKONIUM CHLORIDE 0.12 g/100 mL
INACTIVE INGREDIENTS: ALOE BARBADENSIS LEAF; GLYCERIN; ALPHA-TOCOPHEROL ACETATE; POLYSORBATE 20; WATER; EDETATE DISODIUM; CITRIC ACID; POTASSIUM SORBATE

0282-Total Solutions Alcohol-Free Hand Sanitizing Foam

Active ingredient

Benzalkonium Chloride 0.12%

Purpose

Antiseptic

Uses

- For handwashing to decrease bacteria on the skin.
- After changing diapers.
- After assisting ill persons.
- Before contact with a person under medical care or treatment.
- Recommended for repeat use.

Warnings

For external use only.

Do not use

in the eyes.

When using this product

do not get into eyes. If contact occurs, rinse thoroughly with water.

Stop use and ask a doctor if

irritation and redness develop. If condition persists for more that 72 hours consult a doctor.

Keep out of reach of children.

If swallowed, get medical help or contact a Poison Control Center right away.

Directions

- Wet hands thoroughly with product and allow to dry.
- Children under six years of age should be supervised whtn using this product.

Other information

- Store in a cool, dry place.

Inactive ingredients

Water, Aloe Barbadensis Leaf Juice, Polysorbate 20, Glycerin, Potassium Sorbate, Fragrance, Citric Acid, Disodium EDTA, Tocopheryl Acetate (Vitamin E).